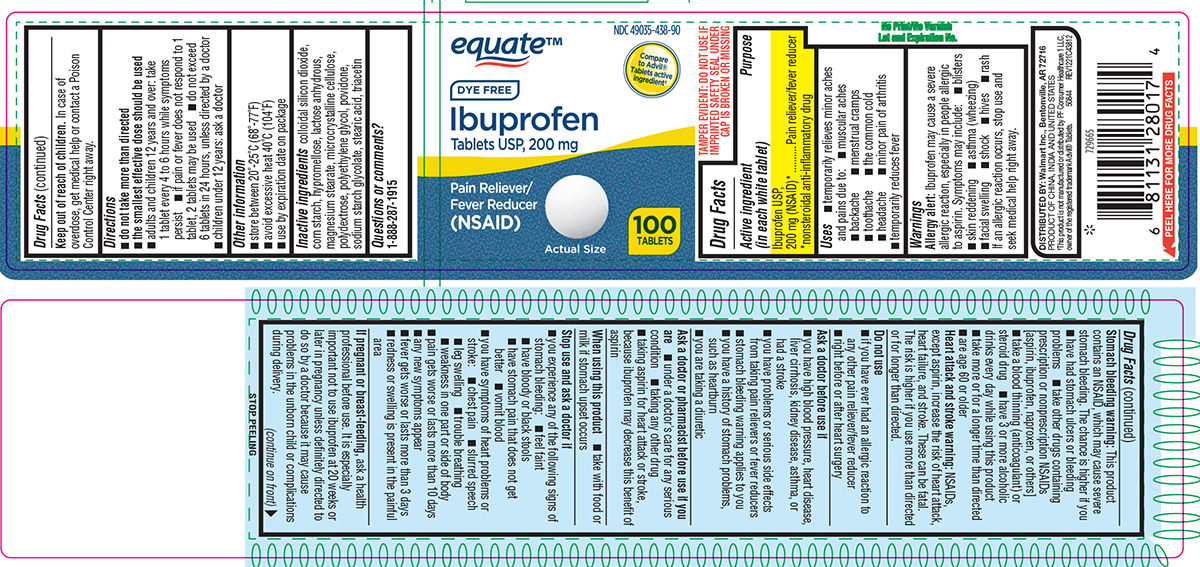 DRUG LABEL: Ibuprofen
NDC: 49035-438 | Form: TABLET, FILM COATED
Manufacturer: Wal-Mart Stores Inc
Category: otc | Type: HUMAN OTC DRUG LABEL
Date: 20250918

ACTIVE INGREDIENTS: IBUPROFEN 200 mg/1 1
INACTIVE INGREDIENTS: SILICON DIOXIDE; STARCH, CORN; HYPROMELLOSE, UNSPECIFIED; ANHYDROUS LACTOSE; MAGNESIUM STEARATE; MICROCRYSTALLINE CELLULOSE; POLYDEXTROSE; POLYETHYLENE GLYCOL, UNSPECIFIED; POVIDONE, UNSPECIFIED; SODIUM STARCH GLYCOLATE TYPE A POTATO; STEARIC ACID; TRIACETIN

Equate 44-438

Active ingredient (in each white tablet)

Ibuprofen USP, 200 mg (NSAID)*
*nonsteroidal anti-inflammatory drug

Purpose

Pain reliever/fever reducer

Uses

- temporarily relieves minor aches and pains due to:
  - headache
  - toothache
  - backache
  - menstrual cramps
  - the common cold
  - muscular aches
  - minor pain of arthritis
- temporarily reduces fever

Warnings

Allergy alert: Ibuprofen may cause a severe allergic reaction, especially in people allergic to aspirin. Symptoms may include:

- blisters
- skin reddening
- asthma (wheezing)
- facial swelling
- shock
- hives
- rash

If an allergic reaction occurs, stop use and seek medical help right away.

Stomach bleeding warning: This product contains an NSAID, which may cause severe stomach bleeding. The chance is higher if you

- have had stomach ulcers or bleeding problems
- take other drugs containing prescription or nonprescription NSAIDs [aspirin, ibuprofen, naproxen, or others]
- take a blood thinning (anticoagulant) or steroid drug
- have 3 or more alcoholic drinks every day while using this product
- take more or for a longer time than directed
- are age 60 or older

Heart attack and stroke warning: NSAIDs, except aspirin, increase the risk of heart attack, heart failure, and stroke. These can be fatal. The risk is higher if you use more than directed or for longer than directed.

Do not use

- if you have ever had an allergic reaction to any other pain reliever/fever reducer
- right before or after heart surgery

Ask a doctor before use if

- you have high blood pressure, heart disease, liver cirrhosis, kidney disease, asthma, or had a stroke
- you have problems or serious side effects from taking pain relievers or fever reducers
- stomach bleeding warning applies to you
- you have a history of stomach problems, such as heartburn
- you are taking a diuretic

Ask a doctor or pharmacist before use if you are

- under a doctor's care for any serious condition
- taking aspirin for heart attack or stroke, because ibuprofen may decrease this benefit of aspirin
- taking any other drug

When using this product

- take with food or milk if stomach upset occurs

Stop use and ask a doctor if

- you experience any of the following signs of stomach bleeding:
  - feel faint
  - have bloody or black stools
  - have stomach pain that does not get better
  - vomit blood
- you have symptoms of heart problems or stroke:
  - chest pain
  - slurred speech
  - leg swelling
  - trouble breathing
  - weakness in one part or side of body
- pain gets worse or lasts more than 10 days
- any new symptoms appear
- fever gets worse or lasts more than 3 days
- redness or swelling is present in the painful area

If pregnant or breast-feeding,

ask a health professional before use. It is especially important not to use ibuprofen at 20 weeks or later in pregnancy unless definitely directed to do so by a doctor because it may cause problems in the unborn child or complications during delivery.

Keep out of reach of children.

In case of overdose, get medical help or contact a Poison Control Center right away.

Directions

- do not take more than directed
- the smallest effective dose should be used
- adults and children 12 years and over: take 1 tablet every 4 to 6 hours while symptoms persist
  - if pain or fever does not respond to 1 tablet, 2 tablets may be used
  - do not exceed 6 tablets in 24 hours, unless directed by a doctor
- children under 12 years: ask a doctor

Other information

- store between 20º-25ºC (68º-77ºF)
- avoid excessive heat 40ºC (104ºF)
- use by expiration date on package

Inactive ingredients

colloidal silicon dioxide, corn starch, hypromellose, lactose anhydrous, magnesium stearate, microcrystalline cellulose, polydextrose, polyethylene glycol, povidone, sodium starch glycolate, stearic acid, triacetin

Questions or comments?

1-888-287-1915

Principal display panel

NDC 49035-438-90

equate™

Compare
to Advil®
Tablets active
ingredient†

DYE FREE

Ibuprofen
Tablets USP, 200 mg

Pain Reliever/
Fever Reducer
(NSAID)

Actual Size

100
TABLETS

TAMPER EVIDENT: DO NOT USE IF
IMPRINTED SAFETY SEAL UNDER
CAP IS BROKEN OR MISSING

DISTRIBUTED BY: Walmart Inc., Bentonville, AR 72716
PRODUCT OF CHINA, INDIA AND UNITED STATES
†This product is not manufactured or distributed by PF Consumer Healthcare 1 LLC,
owner of the registered trademark Advil® Tablets. 50844 REV1221C43812

Equate 44-438